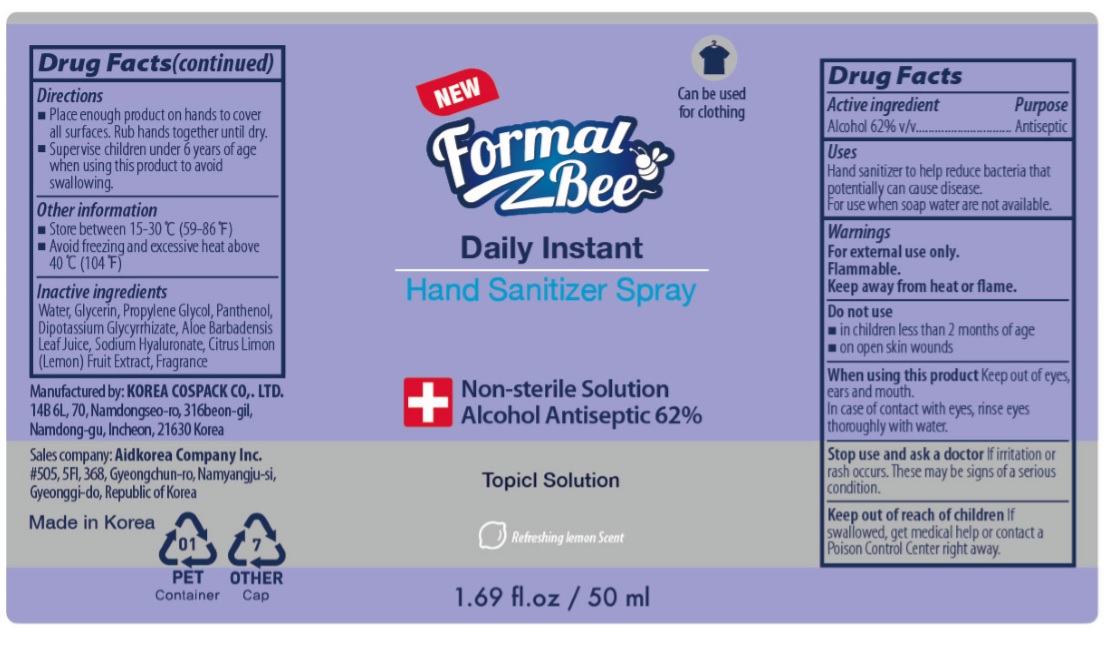 DRUG LABEL: Formal Bee Daily Instant Hand SanitizerSpray
NDC: 74064-2050 | Form: SPRAY
Manufacturer: KOREA COSPACK CO.,LTD.
Category: otc | Type: HUMAN OTC DRUG LABEL
Date: 20200415

ACTIVE INGREDIENTS: ALCOHOL 31 mL/50 mL
INACTIVE INGREDIENTS: GLYCERIN; WATER; PROPYLENE GLYCOL; PANTHENOL; GLYCYRRHIZINATE DIPOTASSIUM; ALOE VERA LEAF; HYALURONATE SODIUM; LEMON

[Formal Bee Daily Instant Hand Sanitizer Spray] 50 ml : 74064-2050